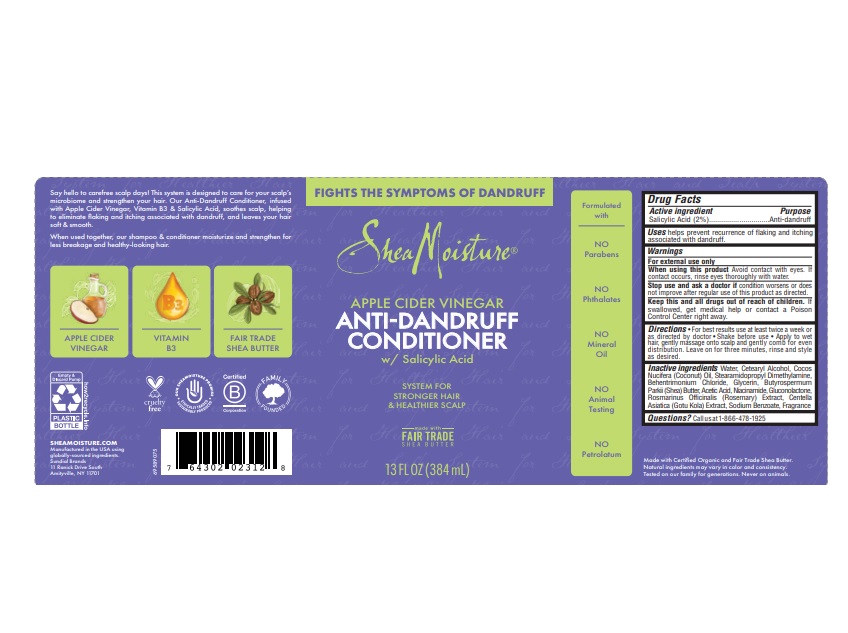 DRUG LABEL: Shea Moisture
NDC: 64942-2083 | Form: LIQUID
Manufacturer: Conopco, Inc. d/b/a/ Unilever
Category: otc | Type: HUMAN OTC DRUG LABEL
Date: 20241107

ACTIVE INGREDIENTS: SALICYLIC ACID 2 g/100 mL
INACTIVE INGREDIENTS: SODIUM BENZOATE; STEARAMIDOPROPYL DIMETHYLAMINE; SHEA BUTTER; WATER; CETOSTEARYL ALCOHOL; BEHENTRIMONIUM CHLORIDE; COCONUT OIL; ACETIC ACID; GLYCERIN; NIACINAMIDE; GLUCONOLACTONE; ROSA DAMASCENA FLOWER

Shea Moisture Apple Cider Vinegar Anti-dandruff Conditioner

Drug Facts

Active ingredient

Salicylic Acid (2%)

Purpose

Anti-dandruff

Uses

Helps prevent recurrence of flaking and itching associated with dandruff.

Warnings

For external use only

When using this product avoid contact with eyes. If contact occurs, rinse eyes thoroughtly with water.

Stop use and ask a doctor if condition worsens or does not improve after regular use of this product as directed.

KEEP OUT OF REACH OF CHILDREN

Keep this and all drugs out of reach of children.

If swallowed, get medical help or contact a Poison Control Center right away.

Directions

For best results use at least twice per week or as directed by a doctor. Shake before use. Apply to wet hair, gently massage onto scalp and gently comb for even distribution. Leave on for three minutes, rinse and style as desired.

Inactive Ingredients

Water, Cetearyl Alcohol, Cocos Nucifera (Coconut) Oil, Stearamidopropyl Dimethylamine, Behentrimonium Chloride, Glycerin, Butyrospermum Parkii (Shea) Butter, Acetic Acid, Niacinamide, Gluconolactone, Rosa Damascena Flower Extract, Centella Asiatica (Gotu Kola) Extract, Sodium Benzoate, Fragrance

Questions?

Call us at 1-866-478-1925